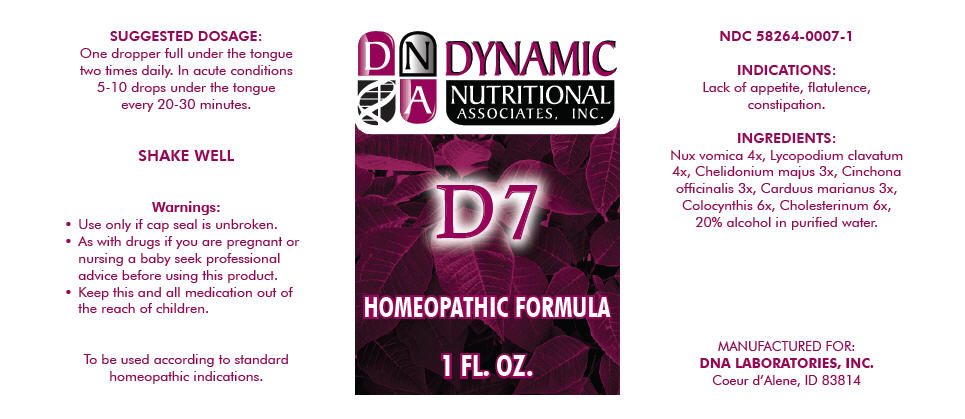 DRUG LABEL: D7
NDC: 58264-0007 | Form: SOLUTION
Manufacturer: DNA Labs, Inc.
Category: homeopathic | Type: HUMAN OTC DRUG LABEL
Date: 20180130

ACTIVE INGREDIENTS: STRYCHNOS NUX-VOMICA SEED 4 [hp_X]/1 mL; LYCOPODIUM CLAVATUM SPORE 4 [hp_X]/1 mL; CHELIDONIUM MAJUS 3 [hp_X]/1 mL; CINCHONA OFFICINALIS WHOLE 3 [hp_X]/1 mL; MILK THISTLE 3 [hp_X]/1 mL; CITRULLUS COLOCYNTHIS WHOLE 6 [hp_X]/1 mL; CHOLESTEROL 6 [hp_X]/1 mL
INACTIVE INGREDIENTS: Alcohol; Water

D7

NDC 58264-0007-1

INDICATIONS AND USAGE

INDICATIONS

Lack of appetite, flatulence, constipation.

ACTIVE INGREDIENT

INGREDIENTS

Nux vomica 4x, Lycopodium clavatum 4x, Chelidonium majus 3x, Cinchona officinalis 3x, Carduus marianus 3x, Colocynthis 6x, Cholesterinum 6x, 20% alcohol in purified water.

SUGGESTED DOSAGE

One dropper full under the tongue two times daily. In acute conditions 5-10 drops under the tongue every 20-30 minutes.

STORAGE AND HANDLING

SHAKE WELL

Warnings

- Use only if cap seal is unbroken.

PREGNANCY OR BREAST FEEDING

- As with drugs if you are pregnant or nursing a baby seek professional advice before using this product.

KEEP OUT OF REACH OF CHILDREN

- Keep this and all medication out of the reach of children.

To be used according to standard homeopathic indications.

PRINCIPAL DISPLAY PANEL - 1 FL. OZ. Bottle Label

DYNAMIC
NUTRITIONAL
ASSOCIATES, INC.

D 7

HOMEOPATHIC FORMULA

1 FL. OZ.